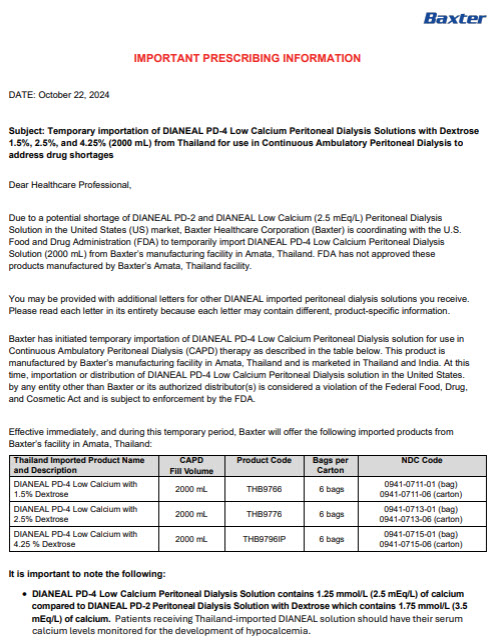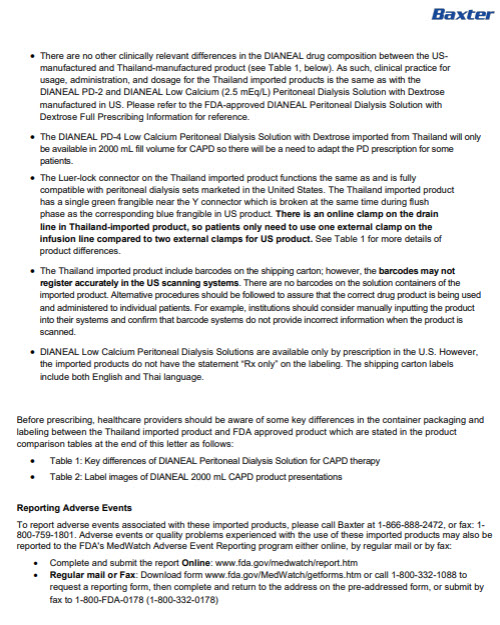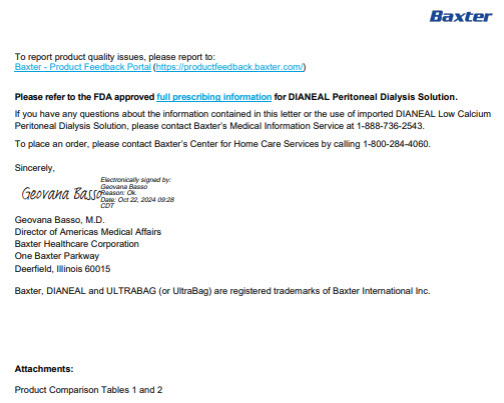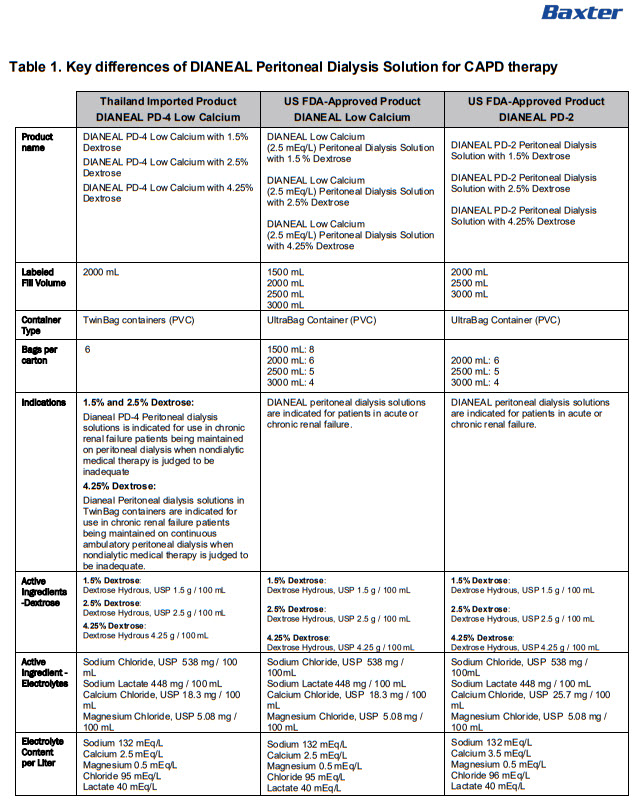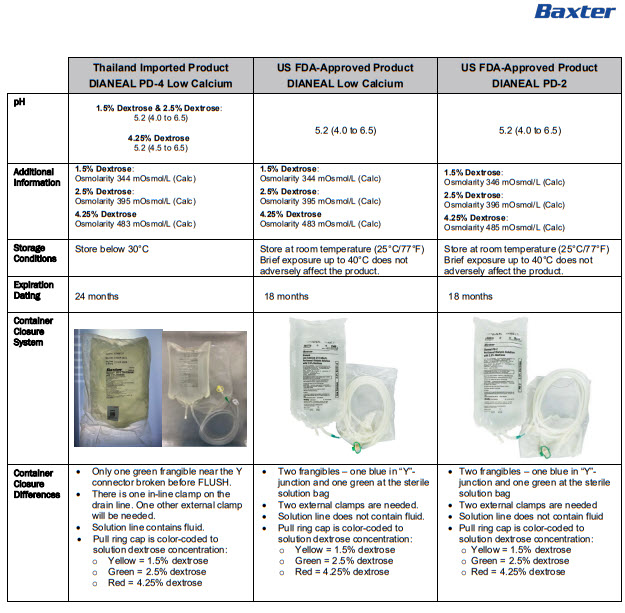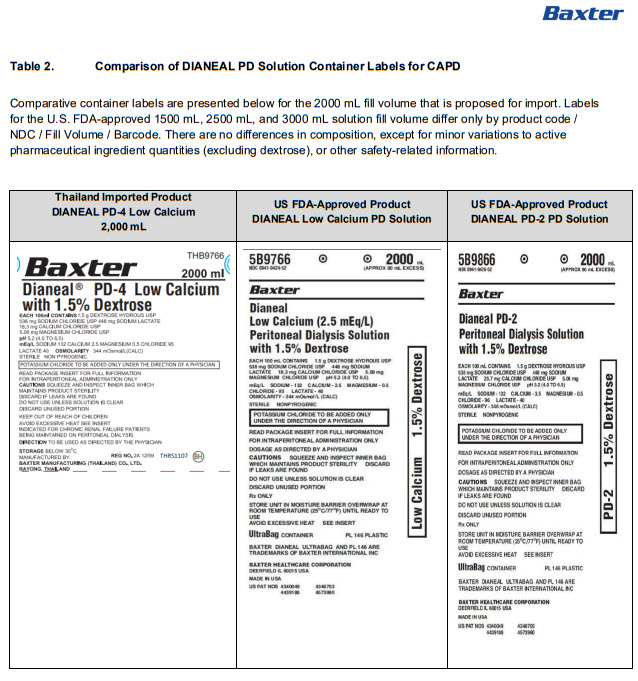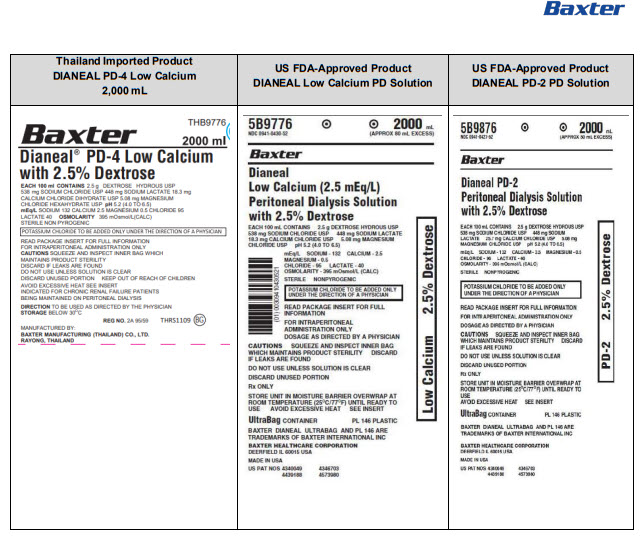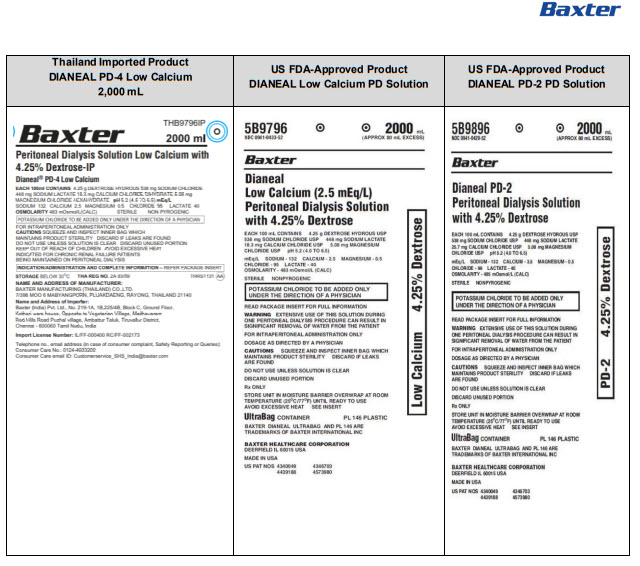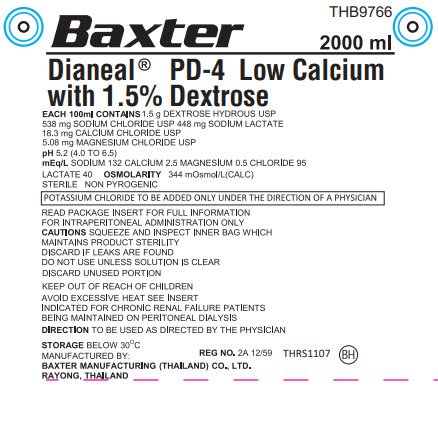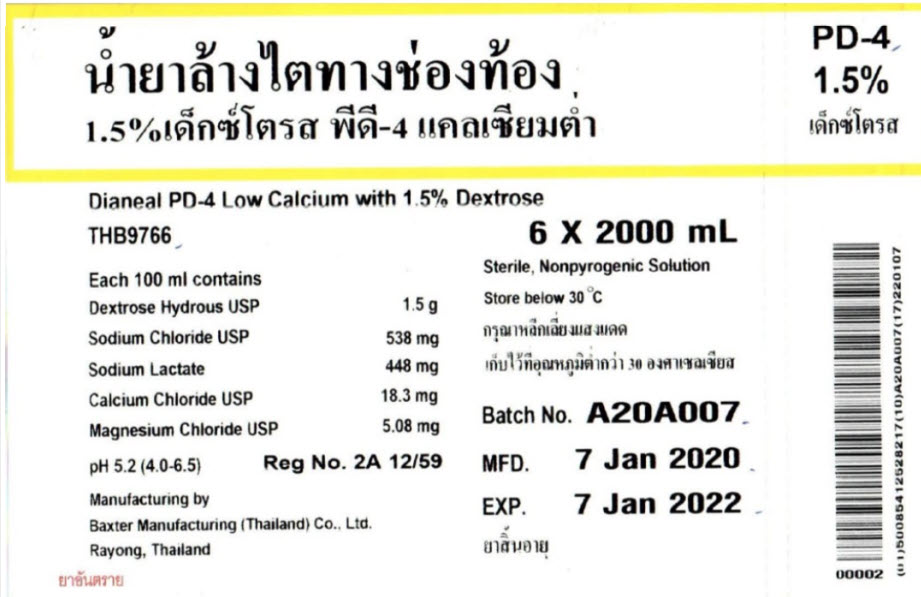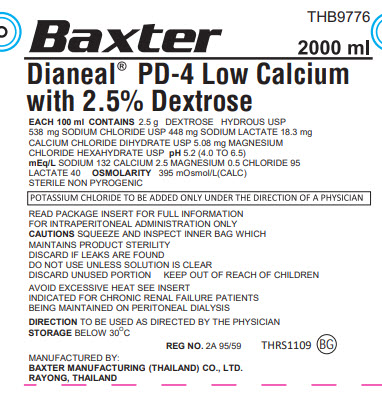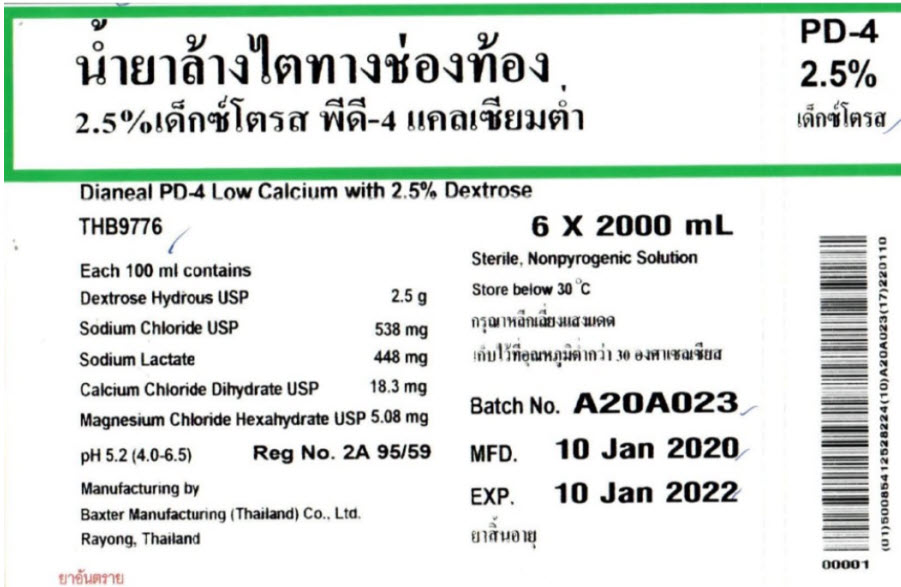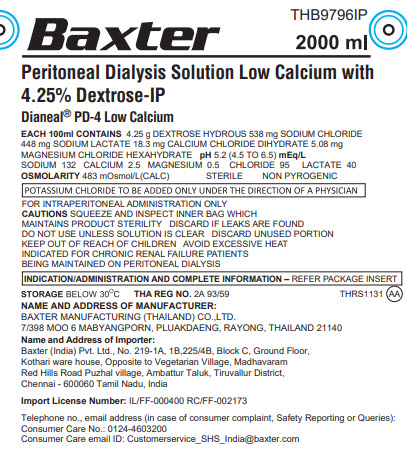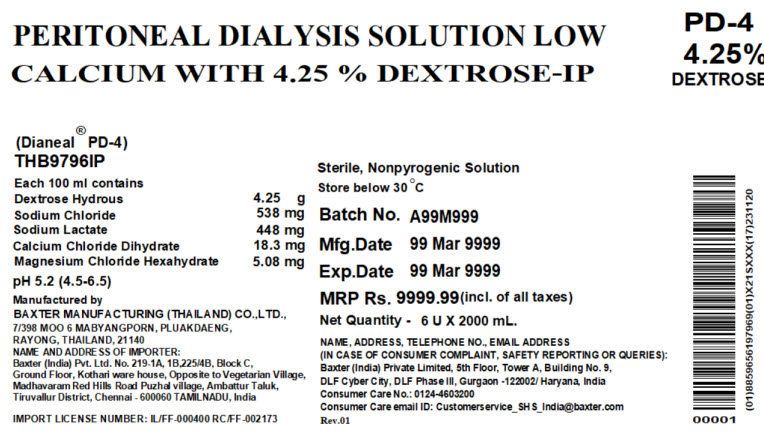 DRUG LABEL: DIANEAL LOW CALCIUM WITH DEXTROSE
NDC: 0941-0711 | Form: INJECTION, SOLUTION
Manufacturer: Vantive US Healthcare LLC
Category: prescription | Type: HUMAN PRESCRIPTION DRUG LABEL
Date: 20250507

ACTIVE INGREDIENTS: DEXTROSE MONOHYDRATE 1.5 g/100 mL; SODIUM CHLORIDE 538 mg/100 mL; SODIUM LACTATE 448 mg/100 mL; CALCIUM CHLORIDE 18.3 mg/100 mL; MAGNESIUM CHLORIDE 5.08 mg/100 mL
INACTIVE INGREDIENTS: WATER

DIANEAL LOW CALCIUM WITH DEXTROSE

PACKAGE/LABEL PRINCIPAL DISPLAY PANEL

BaxterLogo
THB9766
2000 ml

Dianeal® PD-4 Low Calcium
with 1.5% Dextrose

EACH 100ml CONTAINS1.5 g DEXTROSE HYDROUS USP
538 mg SODIUM CHLORIDE USP 448 mg SODIUM LACTATE
18.3 mg CALCIUM CHLORIDE USP
5.08 mg MAGNESIUM CHLORIDE USP
pH5.2 (4.0 to 6.5)
mEq/LSODIUM 132 CALCIUM 2.5 MAGNESIUM 0.5 CHLORIDE 95
LACTATE 40 OSMOLARITY344 mOsmol/L(CALC)
STERILE NON PYROGENIC

POTASSIUM CHLORIDE TO BE ADDED ONLY UNDER THE DIRECTION OF A PHYSICIAN

READ PACKAGE INSERT FOR FULL INFORMATION
FOR INTRAPERITONEAL ADMINISTRATION ONLY
CAUTIONSSQUEEZE AND INSPECT INNER BAG WHICH
MAINTAINS PRODUCT STERILITY
DISCARD IF LEAKS ARE FOUND
DO NOT USE UNLESS SOLUTION IS CLEAR
DISCARD UNUSED PORTION

KEEP OUT OF REACH OF CHILDREN

AVOID EXCESSIVE HEAT SEE INSERT
INDICATED FOR CHRONIC RENAL FAILURE PATIENTS
BEING MAINTAINED ON PERITONEAL DIALYSIS

DIRECTIONTO BE USED AS DIRECTED BY THE PHYSICIAN

STORAGEBELOW 30°C
REG NO.2A 12/59
THRS1107
BH Symbol
MANUFACTURED BY:
BAXTER MANUFACTURING (THAILAND) CO. LTD.
RAYONG, THAILAND

PD-4
1.5%

Dianeal PD-4 Low Calcium with 1.5% Dextrose
THB9766
6 X 2000 mL

Each 100 ml contains
Dextrose Hydrous USP 1.5 g
Sodium Chloride USP 538 mg
Sodium Lactate 448 mg
Calcium Chloride USP 18.3 mg
Magnesium Chloride USP 5.08 mg
pH 5.2 (4.0-6.5)

Reg No. 2A 12/59

Manufacturing by
Baxter Manufacturing (Thailand) Co., Ltd.
Rayong, Thailand

Sterile, Nonpyrogenic Solution
Store below 30°C

Batch No. A20A007
MFD. 7 Jan 2020
EXP. 7 Jan 2022

Barcode
00002

(01)50085412528217(10)A20A007(17)220107

BaxterLogo
THB9776
2000 ml

Dianeal® PD-4 Low Calcium
with 2.5% Dextrose

EACH 100 ml CONTAINS2.5 g DEXTROSE HYDROUS USP
538 mg SODIUM CHLORIDE USP 448 mg SODIUM LACTATE 18.3 mg
CALCIUM CHLORIDE DIHYDRATE USP 5.08 mg MAGNESIUM
CHLORIDE HEXAHYDRATE USP pH5.2 (4.0 to 6.5)
mEq/LSODIUM 132 CALCIUM 2.5 MAGNESIUM 0.5 CHLORIDE 95
LACTATE 40 OSMOLARITY395 mOsmol/L(CALC)
STERILE NON PYROGENIC

POTASSIUM CHLORIDE TO BE ADDED ONLY UNDER THE DIRECTION OF A PHYSICIAN

READ PACKAGE INSERT FOR FULL INFORMATION
FOR INTRAPERITONEAL ADMINISTRATION ONLY
CAUTIONSSQUEEZE AND INSPECT INNER BAG WHICH
MAINTAINS PRODUCT STERILITY
DISCARD IF LEAKS ARE FOUND
DO NOT USE UNLESS SOLUTION IS CLEAR
DISCARD UNUSED PORTION KEEP OUT OF REACH OF CHILDREN

AVOID EXCESSIVE HEAT SEE INSERT
INDICATED FOR CHRONIC RENAL FAILURE PATIENTS
BEING MAINTAINED ON PERITONEAL DIALYSIS

DIRECTIONTO BE USED AS DIRECTED BY THE PHYSICIAN
STORAGEBELOW 30°C

REG NO.2A 95/59
THRS1109
BG Symbol

MANUFACTURED BY:
BAXTER MANUFACTURING (THAILAND) CO. LTD.
RAYONG, THAILAND

PD-4
2.5%

Dianeal PD-4 Low Calcium with 2.5% Dextrose
THB9776
6 X 2000 mL

Each 100 ml contains
Dextrose Hydrous USP 2.5 g
Sodium Chloride USP 538 mg
Sodium Lactate 448 mg
Calcium Chloride Dihydrate USP 18.3 mg
Magnesium Chloride Hexahydrate USP 5.08 mg

pH 5.2 (4.0-6.5)

Reg No. 2A 95/59

Manufacturing by
Baxter Manufacturing (Thailand) Co., Ltd.
Rayong, Thailand

Sterile, Nonpyrogenic Solution
Store below 30°C

Batch No. A20A023
MFD. 10 Jan 2020
EXP. 10 Jan 2022

Barcode
00001

(01)500854 12528224(10)A20A023(17)220110

BaxterLogo
THB9796IP
2000 ml

Peritoneal Dialysis Solution Low Calcium with
4.5% Dextrose-IP
Dianeal® PD-4 Low Calcium

EACH 100 ml CONTAINS4.25 g DEXTROSE HYDROUS 538 mg SODIUM CHLORIDE
448 mg SODIUM LACTATE 18.3 mg CALCIUM CHLORIDE DIHYDRATE 5.08 mg
MAGNESIUM CHLORIDE HEXAHYDRATE pH5.2 (4.5 to 6.5) mEq/L
SODIUM 132 CALCIUM 2.5 MAGNESIUM 0.5 CHLORIDE 95 LACTATE 40
OSMOLARITY483 mOsmol/L(CALC) STERILE NON PYROGENIC

POTASSIUM CHLORIDE TO BE ADDED ONLY UNDER THE DIRECTION OF A PHYSICIAN

FOR INTRAPERITONEAL ADMINISTRATION ONLY
CAUTIONSSQUEEZE AND INSPECT INNER BAG WHICH
MAINTAINS PRODUCT STERILITY DISCARD IF LEAKS ARE FOUND
DO NOT USE UNLESS SOLUTION IS CLEAR DISCARD UNUSED PORTION
KEEP OUT OF REACH OF CHILDREN AVOID EXCESSIVE HEAT
INDICATED FOR CHRONIC RENAL FAILURE PATIENTS
BEING MAINTAINED ON PERITONEAL DIALYSIS

INDICATION/ADMINISTRATION AND COMPLETE INFORMATION –REFER PACKAGE INSERT

STORAGEBELOW 30°C
THA REG NO.2A 93/59
THRS1131
AA Symbol

NAME AND ADDRESS OF MANUFACTURER:
BAXTER MANUFACTURING (THAILAND) CO., LTD.
7/398 MOO 6 MABYANGPORN, PLUAKDAENG, RAYONG, THAILAND 21140

Name and Address of Importer:
Baxter (India) Pvt. Ltd., No. 219-1A, 1B,225/4B, Block C, Ground Floor,
Kothari ware house, Opposite to Vegetarian Village, Madhavaram
Red Hills Road Puzhal village, Ambattur Taluk, Tiruvallur District,
Chennai – 600060 Tamil Nadu, India

Import License Number:IL/FF-000400 RC/FF-002173

Telephone no., email address (in case of consumer complaint, Safety Reporting or Queries):
Consumer Care No.: 0124-4603200
Consumer Care email ID: Customerservice_SHS_India@baxter.com

PEITONEAL DIALYSIS SOLUTION LOW
CALCIUM WITH 4.25% DEXTROSE-IP

PD-4
4.25%
DEXTROSE

(Dianeal® PD-4)
THB9796IP

Each 100 ml contains
Dextrose Hydrous 4.25 g
Sodium Chloride 538 mg
Sodium Lactate 448 mg
Calcium Chloride Dihydrate 18.3 mg
Magnesium Chloride Hexahydrate 5.08 mg

pH 5.2 (4.5-6.5)

Manufactured by
BAXTER MANUFACTURING (THAILAND) CO., LTD.,
7/398 MOO 6 MABYANGPORN, PLUAKDAENG,
RAYONG, THAILAND, 21140
NAME AND ADDRESS OF IMPORTER:
Baxter (India) Pvt. Ltd. No. 219-1A, 1B,225/4B, Block C,
Ground Floor, Kothari ware house, Opposite to Vegetarian Village,
Madhavaran Red Hills Road Puzhal village, Ambattur Taluk,
Tiruvallur District, Chennai – 600060 TAMILNADU, India

IMPORT LICENSE NUMBER: IL/FF-000400 RC/RF-002173

Sterile, Nonpyrogenic Solution
Store below 30°C

Batch No. A99A999
MFD. 99 Mar 9999
EXP. 99 Mar 9999

MRP Rs. 9999.99(incl. of all taxes)
Net Quality – 6 U X 2000 mL.

NAME, ADDRESS, TELEPHONE NO., EMAIL ADDRESS
(IN CASE OF CONSUMER COMPLAINT, SAFETY REPORTING OR QUERIES):
Baxter (India) Private Limited, 5thFloor, Tower A, Building No. 9,
DLF Cyber City, DLF Phase III, Gurgaon – 122002/ Haryana, India
Consumer Care No.: 0124-4603200
Consumer Care email ID: Customerservice_SHS_India@baxter.com
Rev.01

Barcode
00001

(01)8859656197969(10)X21SXXX(17)231120